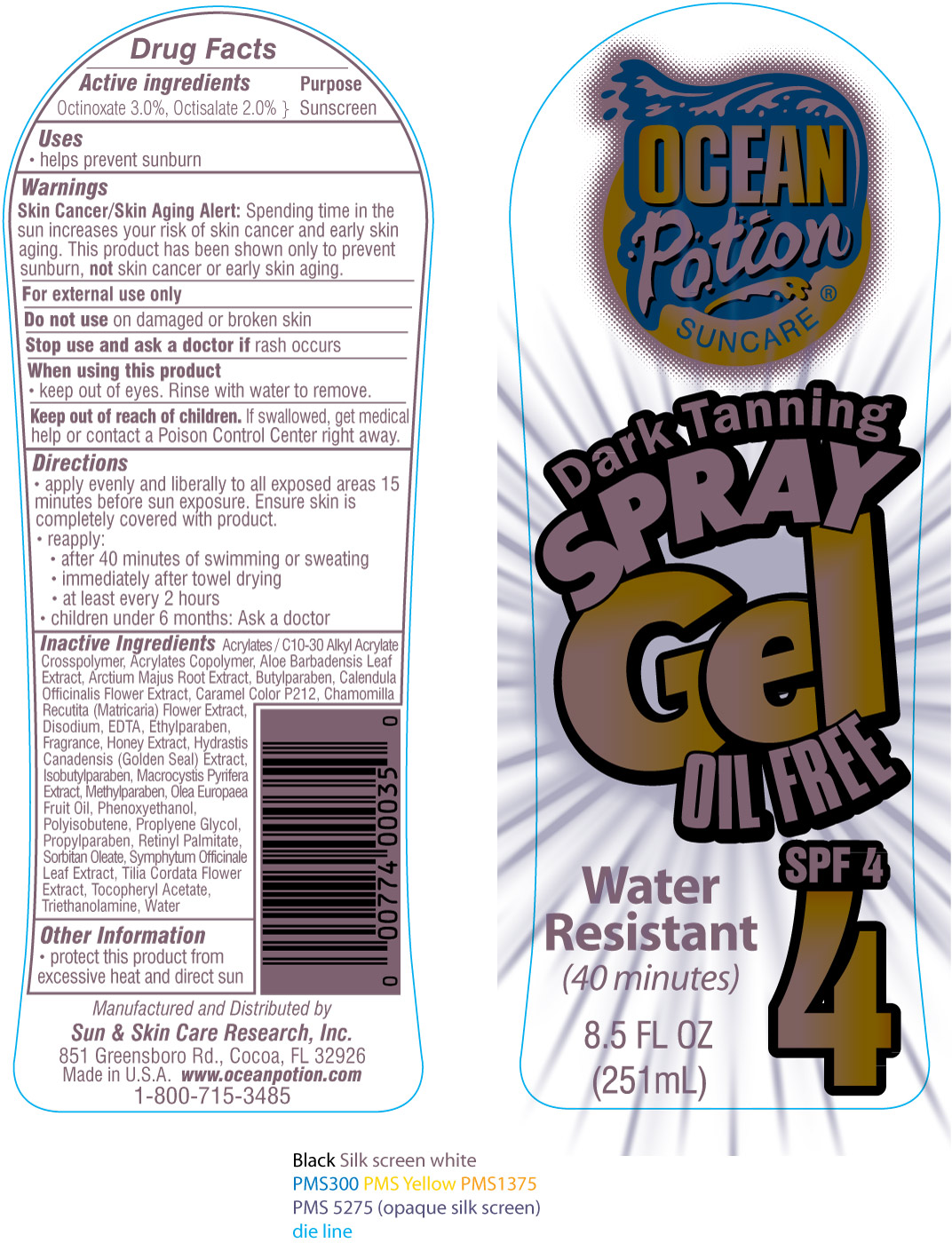 DRUG LABEL: OP Dark Tanning Gel 4
NDC: 62802-035 | Form: SPRAY
Manufacturer: Sun & Skin Care Research, LLC
Category: otc | Type: HUMAN OTC DRUG LABEL
Date: 20120521

ACTIVE INGREDIENTS: OCTINOXATE 3.0 mL/100 mL; OCTISALATE 2.0 mL/100 mL
INACTIVE INGREDIENTS: CARBOMER COPOLYMER TYPE B (ALLYL PENTAERYTHRITOL CROSSLINKED); ALOE VERA LEAF; VITAMIN A PALMITATE; ALPHA-TOCOPHEROL ACETATE; BUTYLPARABEN; EDETATE DISODIUM; ETHYLPARABEN; ISOBUTYLPARABEN; METHYLPARABEN; PHENOXYETHANOL; POLYISOBUTYLENE (2300 MW); PROPYLENE GLYCOL; PROPYLPARABEN; SORBITAN MONOOLEATE; TROLAMINE; WATER; CARAMEL; OLIVE OIL

DRUG FACTS

Active Ingredients

Octinoxate 3.0%
Octisalate 2.0%

Purpose

Sunscreen

Uses

- Helps prevent sunburn

Warnings

Skin Cancer / Skin Aging Alert: Spending time in the sun increases your risk of skin cancer and early skin aging. This product has been shown only to prevent sunburn, not skin cancer or early skin aging.

For external use only. Do not use on damaged or broken skin. Stop use and ask a doctor if rash occurs. When using this product keep out of eyes. Rinse with water to remove. Keep out of the reach of children. If swallowed, get medical help or call a poison control center right away.

Directions

- apply evenly and liberally to all exposed areas 15 minutes before sun exposure. Ensure skin is completely covered with product.
- reapply after 40 minutes of swimming or sweating, immediately after towel drying and at least every 2 hours
- children under 6 months: Ask a doctor

Other Information

- protect this product from excessive heat and direct sun
- for use on skin only
- avoid contact with fabric